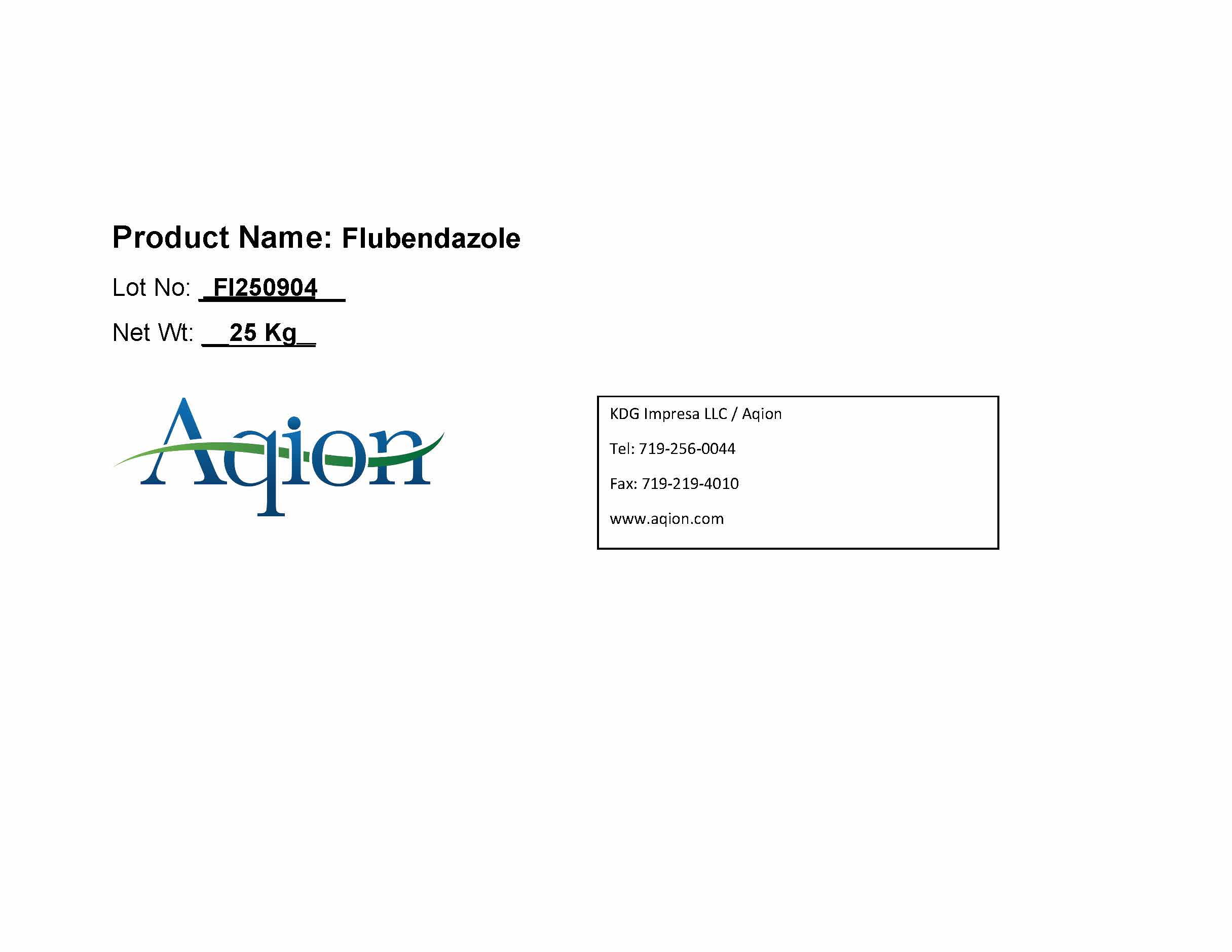 DRUG LABEL: FLUBENDAZOLE
NDC: 43457-654 | Form: POWDER
Manufacturer: KDG Impresa LLC, Aqion
Category: other | Type: BULK INGREDIENT - ANIMAL DRUG
Date: 20251030

ACTIVE INGREDIENTS: FLUBENDAZOLE 1 kg/1 kg

FLUBENDAZOLE

Flubendazole Bulk Product Label

Flubendazole